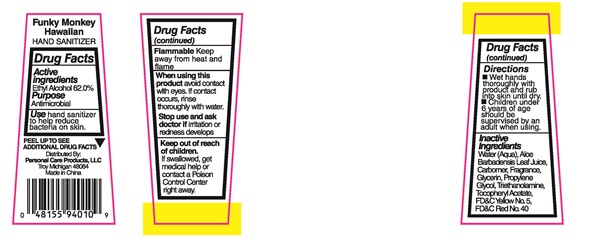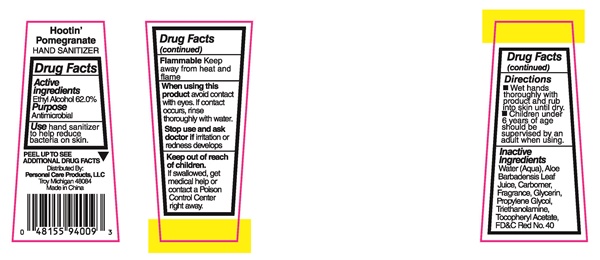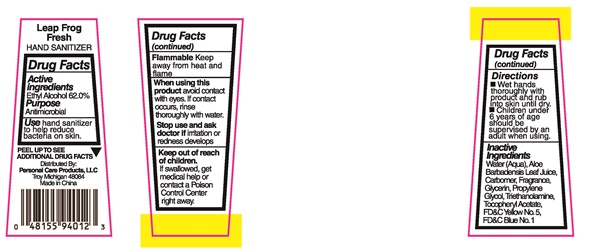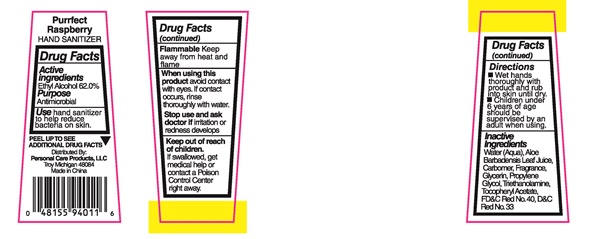 DRUG LABEL: Hootin Pomegranate
NDC: 29500-9409 | Form: LIQUID
Manufacturer: Personal Care Products, LLC
Category: otc | Type: HUMAN OTC DRUG LABEL
Date: 20160512

ACTIVE INGREDIENTS: ALCOHOL 17.57 g/30 mL
INACTIVE INGREDIENTS: WATER; ALOE VERA LEAF; CARBOXYPOLYMETHYLENE; GLYCERIN; PROPYLENE GLYCOL; TROLAMINE; .ALPHA.-TOCOPHEROL ACETATE; FD&C RED NO. 40

Funky Monkey- 9410
Leap Frog - 9412
Hootin Pomegranate - 9409
Purrfect Raspberry - 9411

Drug Facts Active ingredients

Ethyl Alcohol 62.0%

Purpose

Antimicrobial

Keep out of reach of children

If swallowed, get medical help or contact a Poison Control Center right away.

Use

hand sanitizer to help reduce bacteria on skin

Warnings

Flammable

Keep away from heat and flame

When using this product

avoid contact with eyes. If contact occurs, rinse thoroughly with water.

Stop use and ask a doctor

if irritation or redness develops

Directions

- Wet hands thoroughly with product and rub into skin until dry.
- Children under 6 years of age should be supervised by an adult when using.

Inactive Ingredients

Water (Aqua) Aloe Barbadensis Leaf Juice, Carbomer, Fragrance, Glycerin, Propylene Glycol, Triethanolamine, Tocopheryl Acetate, FD&C Yellow No.5, FD&C Blue No.1, FD&C Red No.40, D&C Red No.33

Product Label Hootin' Pomegranate Funky Monkey Hawaiian Purrfect Raspberry Leap Frog Fresh

Hootin' Pomegranate HAND SANITIZER

PEEL UP TO SEE ADDITIONAL DRUG FACTS

Distributed By:

Personal Care Products, LLC

Troy Michigan 48084

Made in China

Funky Monkey Hawaiian HAND SANITIZER

PEEL UP TO SEE ADDITIONAL DRUG FACTS

Distributed By:

Personal Care Products, LLC

Troy Michigan 48084

Made in China

Purrfect Raspberry HAND SANITIZER

PEEL UP TO SEE ADDITIONAL DRUG FACTS

Distributed By:

Personal Care Products, LLC

Troy Michigan 48084

Made in China

Leap Frog Fresh HAND SANITIZER

PEEL UP TO SEE ADDITIONAL DRUG FACTS

Distributed By:

Personal Care Products, LLC

Troy Michigan 48084

Made in China